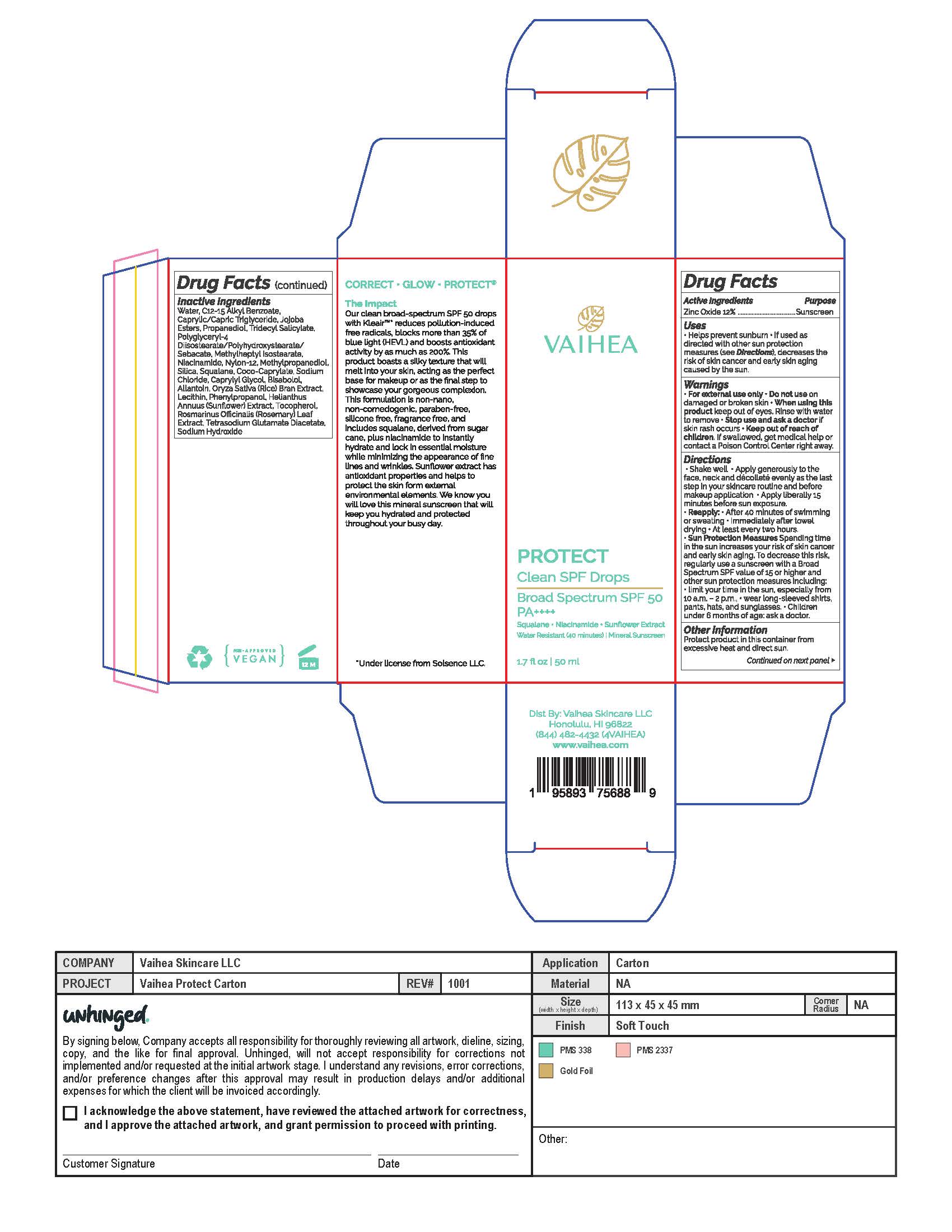 DRUG LABEL: Vaihea Protect Clean SPF Drops
NDC: 83395-050 | Form: LOTION
Manufacturer: Vaihea Skincare LLC
Category: otc | Type: HUMAN OTC DRUG LABEL
Date: 20251106

ACTIVE INGREDIENTS: ZINC OXIDE 132 mg/1 mL
INACTIVE INGREDIENTS: JOJOBA OIL; ORYZA SATIVA WHOLE; TRIDECYL SALICYLATE; SILICON DIOXIDE; TOCOPHEROL; CAPRYLYL GLYCOL; PHENYLPROPANOL; SQUALANE; COCO-CAPRYLATE; NYLON-12; HELIANTHUS ANNUUS FLOWERING TOP; LECITHIN, SOYBEAN; METHYLHEPTYL ISOSTEARATE; METHYLPROPANEDIOL; ALLANTOIN; ALKYL (C12-15) BENZOATE; ROSMARINUS OFFICINALIS FLOWER; .ALPHA.-BISABOLOL, (+)-; SODIUM HYDROXIDE; WATER; NIACINAMIDE; PROPANEDIOL; TETRASODIUM GLUTAMATE DIACETATE; SODIUM CHLORIDE; POLYGLYCERYL-4 DIISOSTEARATE/POLYHYDROXYSTEARATE/SEBACATE

Vaihea Protect Clean SPF Drops